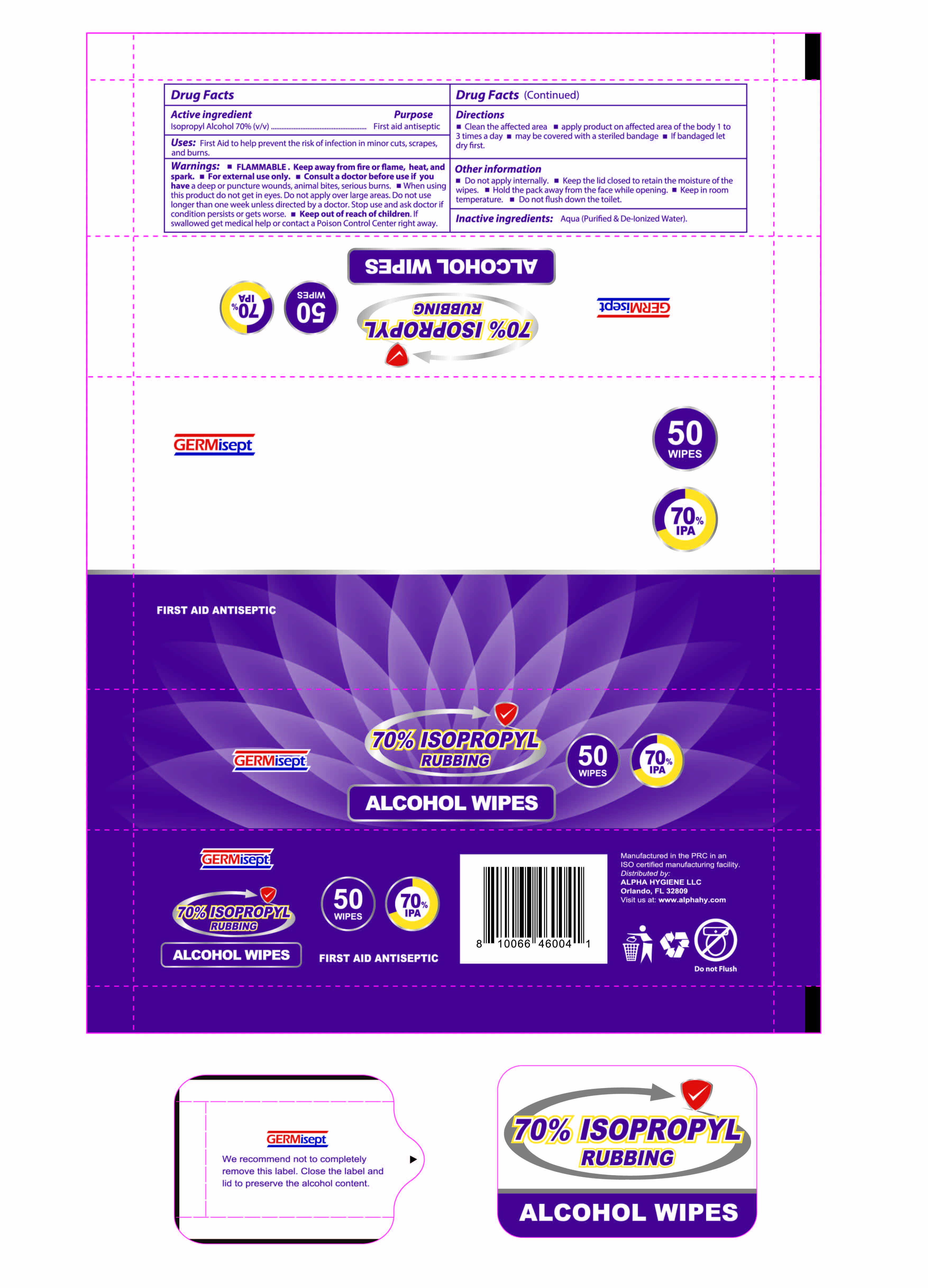 DRUG LABEL: 70% ISOPROPYL RUBBING ALCOHOL WIPES
NDC: 75127-009 | Form: CLOTH
Manufacturer: Jurong Dongfa General Merchandise Co., Ltd.
Category: otc | Type: HUMAN OTC DRUG LABEL
Date: 20220224

ACTIVE INGREDIENTS: ISOPROPYL ALCOHOL 0.7 g/1 g
INACTIVE INGREDIENTS: WATER

75127-009 70% ISOPROPYL RUBBING ALCOHOL WIPES

Active ingredient

lsopropyl Alcohol 70%(v/)

Purpose

First aid antiseptic

Uses:

First Aid to help prevent the risk of infection in minor cuts, scrapes,and burns.

Warnings

FLAMMABLE.Keep away from fire or flame, heat, anspark. For external use only. Consult a doctor before use if youhave a deep or puncture wounds, animal bites,serious burns.m When usingthis product do not get in eyes. Do not apply over large areas. Do not uselonger than one week unless directed by a doctor. Stop use and ask doctor ifcondition persists or gets worse. Keep out of reach of children. If swallowed get medical help or contact a Poison Control Center right away.

Keep this out of reach of children.

- unless under adult supervision.
- If swallowed, get medical help or contact a Poison Control Center immediately.

Directions

Clean the affected area apply product on affected area of the body 1 to3 times a day m may be covered with a steriled bandage m lf bandaged let dry first.

Other information

Do not apply internally. m Keep the lid closed to retain the moisture of the wipes. Hold the pack away from the face while opening. Keep in room temperature. Do not flush down the toilet.

Inactive ingredients

Aqua(Purified & De-lonized Water).